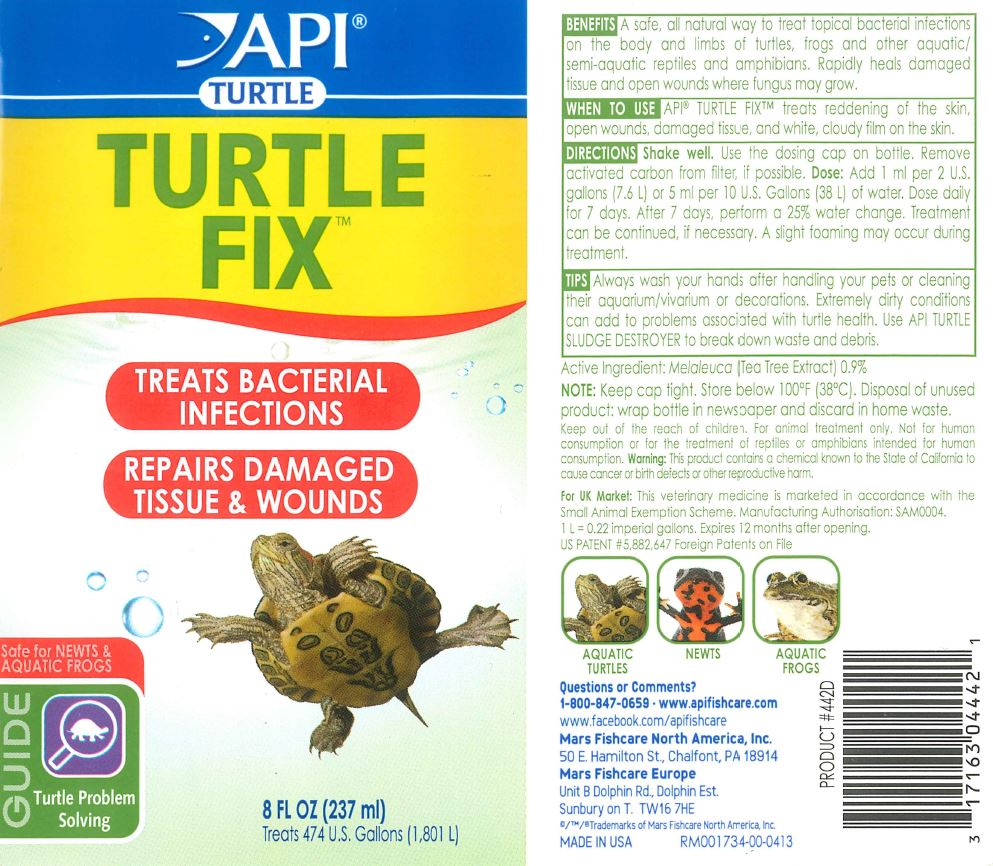 DRUG LABEL: API TURTLE TURTLE FIX
NDC: 17163-442 | Form: LIQUID
Manufacturer: MARS FISHCARE NORTH AMERICA, INC.
Category: animal | Type: OTC ANIMAL DRUG LABEL
Date: 20191219

ACTIVE INGREDIENTS: CAJUPUT OIL 0.9 g/100 mL

Drug Label

DESCRIPTION

BENEFITS

A safe, all natural way to treat topical bacterial infections on the body and limbs of turtles, frogs and other aquatic/semi-aquatic reptiles and amphibians.

Rapidly heals damaged tissue and open wounds where fungus may grow.

INDICATIONS AND USAGE

WHEN TO USE

API TURTLE FIX treats reddening of the skin, open wounds, damaged tissue, and white, cloudy film on the skin.

DIRECTIONS

Shake well.

Use the dosing cap on the bottle.

Remove activated carbon from filter, if possible.

Dose: Add 1 ml per 2 U.S. gallons (7.6 L) or 5 ml per 10 U.S. Gallons (38 L) of water.

Dose daily for 7 days.

After 7 days, perform a 25% water change.

Treatment can be continued, if necessary.

A slight foaming may occur during treatment.

GENERAL PRECAUTIONS

TIPS

Always wash your hands after handling your pets or cleaning their aquarium/vivarium or decorations.

Extremely dirty conditions can add to problems associated with turtle health.

Use API TURTLE SLIDGE DESTROYER to break down waste and debris.

Active Ingredient: Melaleuca (Tea Tree Extract) 0.9%

STORAGE AND HANDLING

NOTE: Keep cap tight.

Store below 100 F (38 C).

Disposal of unused product: wrap bottle in newspaper and discard in home waste.

Keep out of reach of children.

For animal treatment only.

Not for human consumption or for the treatment of reptiles or amphibians intended for human consumption.

Warning: This product contains a chemical known to the State of California to cause cancer or birth defects or other reproductive harm.

For UK Market: This veterinary medicine is marketed in accordance with the Small Animal Exemption Scheme. Manufacturing Authorization" SAM0004.

1 L = 0.22 imperial gallons. Expires 12 months after opening. US PATENT 5,882,647 Foreign Patents on File

AQUATIC TURTLES

NEWTS

AQUATIC FROGS

Questions or Comments?

1-800-847-0659

www.apifishcare.com

www.facebook.com/apifishcare

PACKAGE LABEL

API

TURTLE

TURTLE

FIX

TREATS BACTERIAL

INFECTIONS

REPAIRS DAMAGED

TISSUE and WOUNDS

Safe for NEWTS and

AQUATIC FROGS

GUIDE

Turtle Problem

Solving

8 FL OZ (237 ml)

Treats 474 U.S. Gallons (1, 801 L)